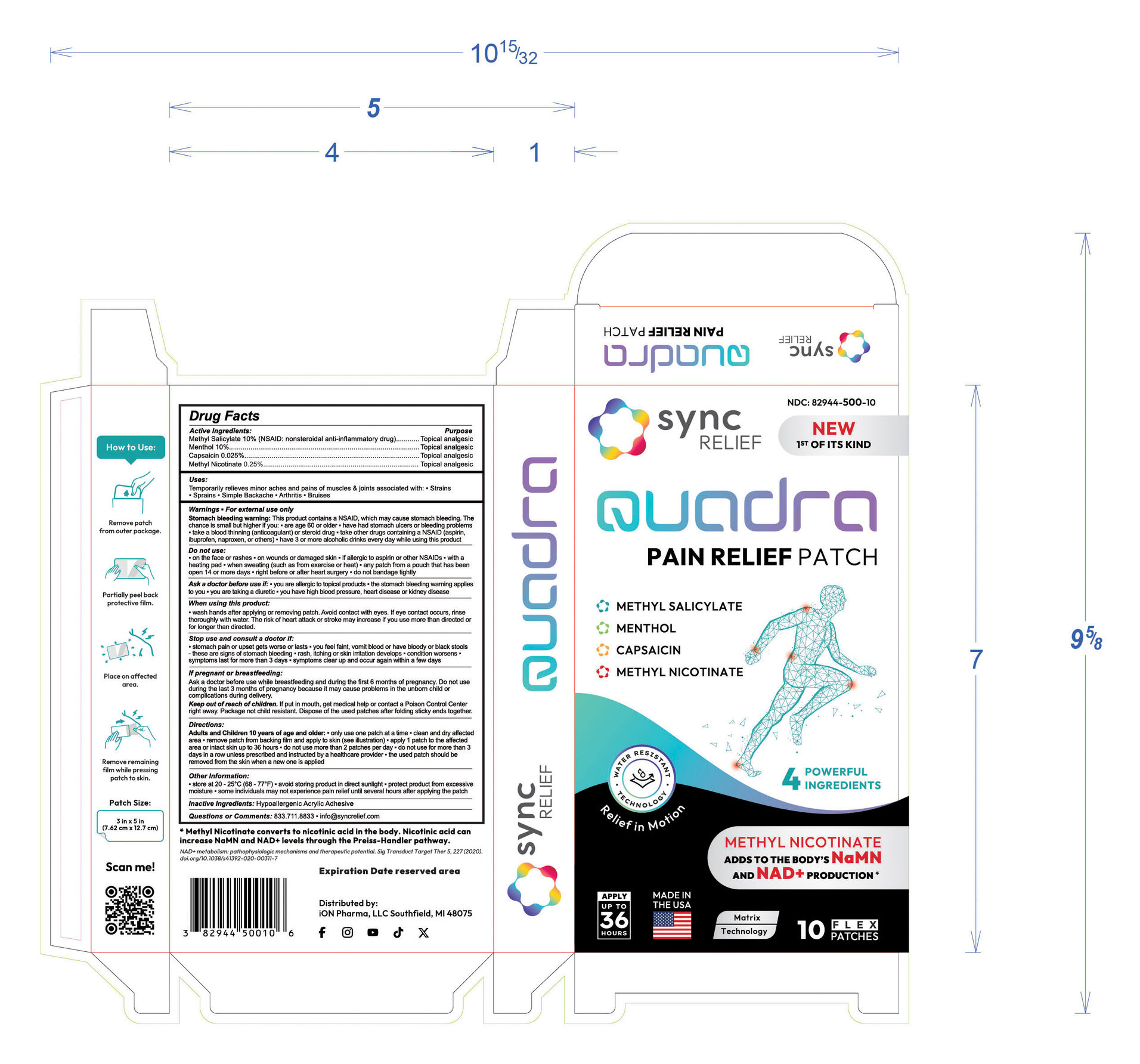 DRUG LABEL: Sync Quadra
NDC: 82944-500 | Form: PATCH
Manufacturer: Ion Pharma, LLC
Category: otc | Type: HUMAN OTC DRUG LABEL
Date: 20250728

ACTIVE INGREDIENTS: MENTHOL 10 g/1 1; CAPSAICIN 0.025 g/1 1; METHYL NICOTINATE 0.25 g/1 1; METHYL SALICYLATE 10 g/1 1
INACTIVE INGREDIENTS: ACRYLIC ACID

Sync Relief Quadra (Methyl salicylate 10%, Menthol 10%, Capsaicin 0.025%, Methyl nicotinate 0.25%)

Drug facts

Active ingredients (in each patch)...... Purpose
Menthol 10% ............................................. Topical analgesic
Methyl salicylate 10% .............................. Topical analgesic
Capsaicin 0.025% ................................. Topical analgesic
Methyl nicotinate 0.25% ............................. Topical analgesic

Uses section

Uses:

Temporarily relieves minor aches and pains of muscles & joints associated with:

- Strains
- Sprains
- Simple Backache
- Arhtritis
- Bruises

NSAID warning, Do not use section

For external use only
Stomach bleeding warning: This product contains a NSAID, which may cause stomach bleeding. The chance is small but higher if you:

- are age 60 or older
- have had stomach ulcers or bleeding problems
- take a blood thinning (anticoagulant) or steroid drug
- take other drugs containing NSAID (aspirin, ibuprofen, naproxen, or others)
- have 3 or more alcoholic drinks every day while using this product

Do not use:

- on the face or rashes
- on wounds or damaged skin
- if allergic to aspirin or other NSIADs
- with a heating pad
- when sweating (such as from exercise or heat)
- any patch from a pouch that has been open 14 days or more days
- right before or after heart surgery
- do not bandage tightly

When using this product

wash hands after applying or removing patch. Avoid contact with eyes. If eye contact occurs, rinse thoroughly with water. The risk of heart attack or stroke may increase if you use more than directed or for longer than directed.

Stop use section

Stop use and ask a doctor if

- condition worsens
- symptoms last for more than 7 days or clear up and occur again within a few days
- you experience signs of stomach bleeding, such as feeling faint, vomiting blood, or have bloody or black stools
- redness or swelling occurs
- a burning sensation occurs

If pregnant or breast-feeding section

Ask a doctor before use while breastfeeding and during the first 6 months of pregnancy. Do not use during the last 3 months of pregnancy because it may cause problems in the unborn child or complications during delivery.

Keep out of reach of children section

If put in mouth, get medical help or contact a Poison Control Center right away. Package not child resistant. Dispose of the used patches after folding sticky ends together.

Directions section

Adults and children 10 years of age and older:

only use one patch at a time
clean and dry affected area
remove patch from backing film and apply to skin (see illustration)
apply 1 patch to the affected area or intact skin up to 36 hours
do not use more than 2 patches per day
do not use for more than 3 days in a row unless prescribed and instructed by a healthcare provider
the used patch should be removed from the skin when a new one is applied

INACTIVE INGREDIENT

Hypoallergenic acrylic adhesive

Questions or comments section

Questions or Comments:

833.711.8833

info@syncrelief.com

PACKAGE LABEL

NDC: 82944-500-10

NEW 1st OF ITS KIND

Quadra

PAIN RELIEF PATCH

METHYL SALICYLATE

MENTHOL

CAPSAICIN

METHYL NICOTINATE

WATER RESISTANT TECHNOLOGY

Relief in Motion

4 POWERFUL INGREDIENTS

METHYL NICOTINATE ADDS TO THE BODY'S NaMN AND NAD+ PRODUCTION*

APPLY UP TO 36 HOURS
MADE IN THE USA

MATRIX TECHNOLOGY

10 FLEX PATCHES